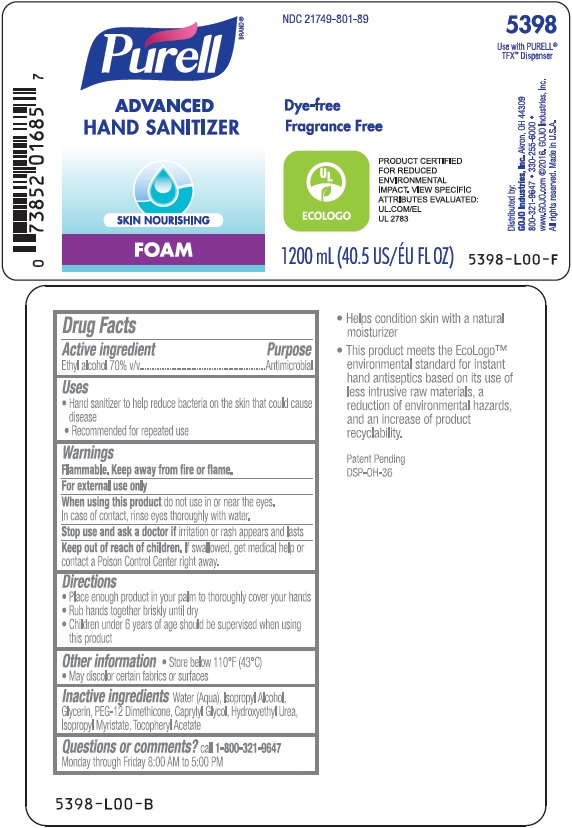 DRUG LABEL: PURELL Advanced Skin Nourishing Instant Hand Sanitizer
NDC: 21749-801 | Form: LIQUID
Manufacturer: GOJO Industries, Inc.
Category: otc | Type: HUMAN OTC DRUG LABEL
Date: 20241212

ACTIVE INGREDIENTS: ALCOHOL 0.7 mL/1 mL
INACTIVE INGREDIENTS: WATER; ISOPROPYL ALCOHOL; GLYCERIN; PEG-12 DIMETHICONE; CAPRYLYL GLYCOL; HYDROXYETHYL UREA; ISOPROPYL MYRISTATE; ALPHA-TOCOPHEROL ACETATE

PURELL Advanced Skin Nourishing Hand Sanitizer Foam

Active Ingredient

Ethyl Alcohol 70% v/v

Purpose

Antimicrobial

Use

Hand sanitizer to help reduce bacteria on the skin that could cause disease

Directions

- Place enough product in your palm to thoroughly cover your hands
- Rub hands together briskly until dry
- Children under 6 years of age should be supervised when using this product

Warnings Flammable. Keep away from fire or flame.

For external use only

WHEN USING

When using this productdo not use in or near the eyes. In case of contact, rinse eyes thoroughly with water.

Stop use and ask a doctor ifirritation or rash appears and lasts

Keep out of reach of children.If swallowed, get medical help or contact a Poison Control Center right away.

Inactive ingredients

Water (Aqua), Isopropyl Alcohol, Glycerin, PEG-12 Dimethicone, Caprylyl Glycol, Hydroxyethyl Urea, Isopropyl Myristate, Tocopheryl Acetate